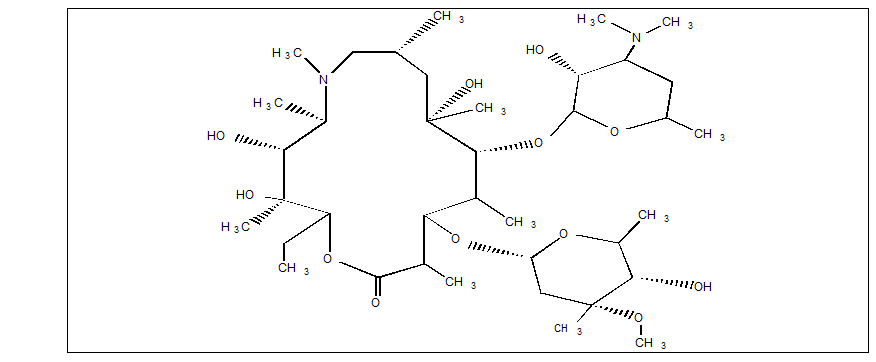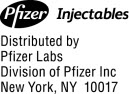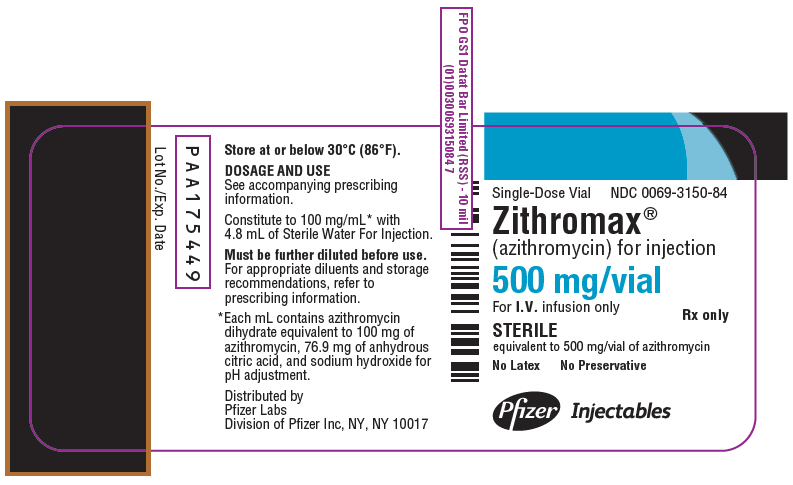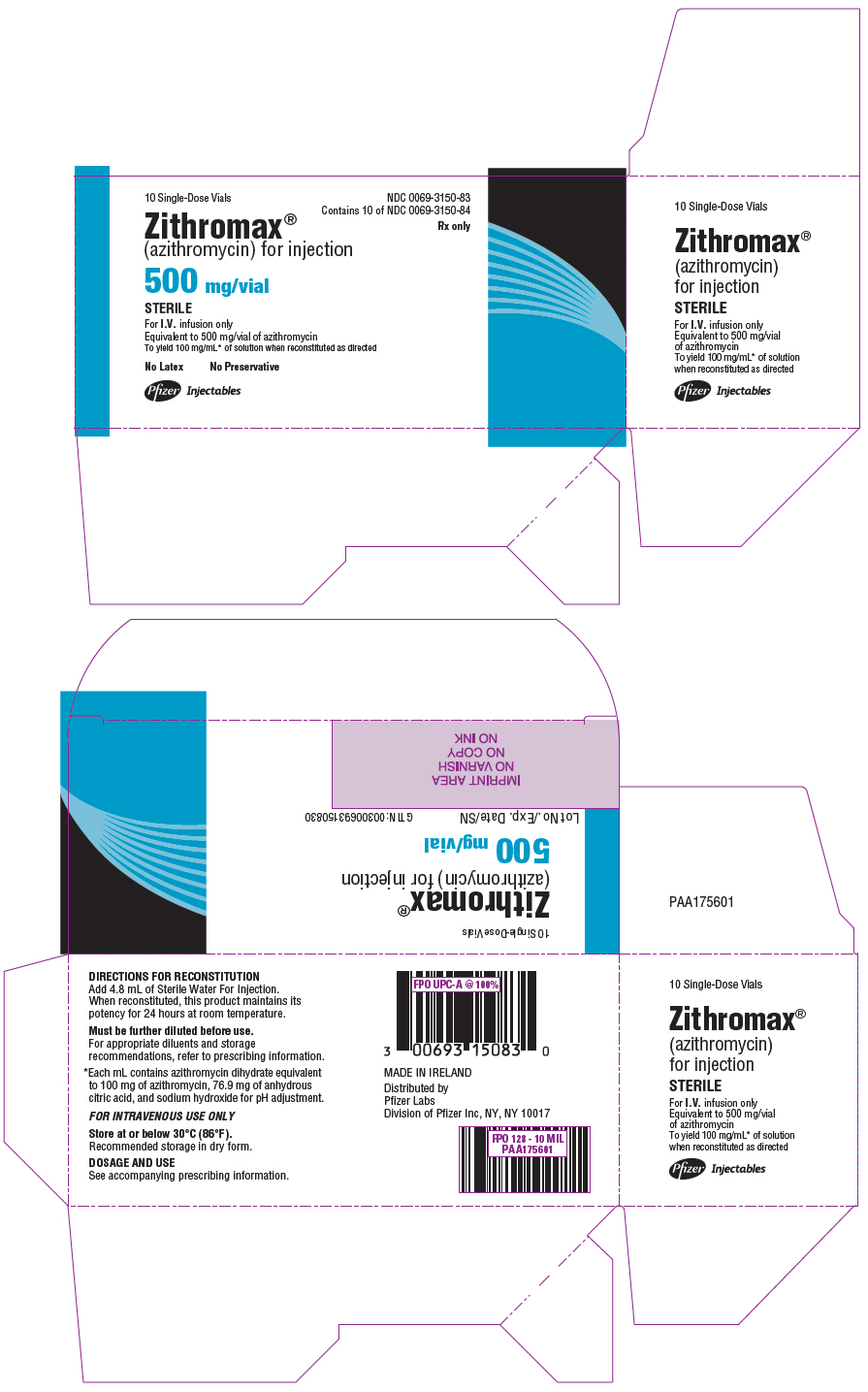 DRUG LABEL: Zithromax
NDC: 0069-3150 | Form: INJECTION, POWDER, LYOPHILIZED, FOR SOLUTION
Manufacturer: Pfizer Laboratories Div Pfizer Inc
Category: prescription | Type: HUMAN PRESCRIPTION DRUG LABEL
Date: 20250218

ACTIVE INGREDIENTS: AZITHROMYCIN DIHYDRATE 500 mg/5 mL
INACTIVE INGREDIENTS: CITRIC ACID MONOHYDRATE; SODIUM HYDROXIDE

HIGHLIGHTS OF PRESCRIBING INFORMATION

These highlights do not include all the information needed to use ZITHROMAX safely and effectively. See full prescribing information for ZITHROMAX.
ZITHROMAX® (azithromycin) for injection, for intravenous use
Initial U.S. Approval: 1991

RECENT MAJOR CHANGES

Warnings and Precautions, Cardiovascular Death (5.5) | 11/2021

1 INDICATIONS AND USAGE

ZITHROMAX is a macrolide antibacterial drug indicated for mild to moderate infections caused by designated, susceptible bacteria:

- Community-acquired pneumonia in adults (1.1)
- Pelvic inflammatory disease (1.2)

To reduce the development of drug-resistant bacteria and maintain the effectiveness of ZITHROMAX and other antibacterial drugs, ZITHROMAX should be used only to treat or prevent infections that are proven or strongly suspected to be caused by susceptible bacteria. (1.3)

2 DOSAGE AND ADMINISTRATION

- Community-acquired pneumonia: 500 mg as a single daily dose by the intravenous route for at least two days. (2.1)
- Pelvic inflammatory disease in adults: 500 mg as a single daily dose by the intravenous route for one or two days. (2.2)

3 DOSAGE FORMS AND STRENGTHS

ZITHROMAX (azithromycin) for injection is supplied as white to off-white lyophilized powder in a single-dose vial equivalent to 500 mg of azithromycin for intravenous administration. (3)

4 CONTRAINDICATIONS

- Patients with known hypersensitivity to azithromycin, erythromycin, any macrolide, or ketolide antibacterial drug. (4.1)
- Patients with a history of cholestatic jaundice/hepatic dysfunction associated with prior use of azithromycin. (4.2)

5 WARNINGS AND PRECAUTIONS

- Serious (including fatal) allergic and skin reactions. Discontinue ZITHROMAX and initiate appropriate therapy if reaction occurs. (5.1)
- Hepatotoxicity: Severe and sometimes fatal, hepatoxicity has been reported. Discontinue ZITHROMAX immediately if signs and symptoms of hepatitis occur. (5.2)
- Infantile Hypertrophic Pyloric Stenosis (IHPS): Following the use of azithromycin in neonates (treatment up to 42 days of life), IHPS has been reported. Direct parents and caregivers to contact their physician if vomiting or irritability with feeding occurs. (5.3)
- Prolongation of QT interval and cases of torsades de pointes have been reported. This risk which can be fatal should be considered in patients with certain cardiovascular disorders including known QT prolongation or history torsades de pointes, those with proarrhythmic conditions, and with other drugs that prolong the QT interval. (5.4)
- Cardiovascular Death: Some observational studies have shown an approximately two-fold increased short-term potential risk of acute cardiovascular death in adults exposed to azithromycin relative to other antibacterial drugs, including amoxicillin. Consider balancing this potential risk with treatment benefits when prescribing ZITHROMAX. (5.5)
- Clostridioides difficile-Associated Diarrhea: Evaluate patients if diarrhea occurs. (5.6)
- ZITHROMAX may exacerbate muscle weakness in persons with myasthenia gravis. (5.7)

6 ADVERSE REACTIONS

Most common adverse reactions are nausea (4%), diarrhea (4%), abdominal pain (3%), or vomiting (1%). (6)

To report SUSPECTED ADVERSE REACTIONS, contact Pfizer Inc. at 1-800-438-1985 or FDA at 1-800-FDA-1088 or www.fda.gov/medwatch.

7 DRUG INTERACTIONS

- Nelfinavir: Close monitoring for known adverse reactions of azithromycin, such as liver enzyme abnormalities and hearing impairment, is warranted. (7.1)
- Warfarin: Use with azithromycin may increase coagulation times; monitor prothrombin time. (7.2)

8 USE IN SPECIFIC POPULATIONS

- Pediatric use: Safety and effectiveness in the treatment of patients under 16 years of age have not been established. (8.4)
- Geriatric use: Elderly patients may be more susceptible to development of torsades de pointes arrhythmias. (8.5)

FULL PRESCRIBING INFORMATION

1 INDICATIONS AND USAGE

ZITHROMAX (azithromycin) for injection is a macrolide antibacterial drug indicated for the treatment of patients with infections caused by susceptible strains of the designated microorganisms in the conditions listed below.

1.1 Community-Acquired Pneumonia

due to Chlamydophila pneumoniae, Haemophilus influenzae, Legionella pneumophila, Moraxella catarrhalis, Mycoplasma pneumoniae, Staphylococcus aureus, or Streptococcus pneumoniae in patients who require initial intravenous therapy.

1.2 Pelvic Inflammatory Disease

due to Chlamydia trachomatis, Neisseria gonorrhoeae, or Mycoplasma hominis in patients who require initial intravenous therapy. If anaerobic microorganisms are suspected of contributing to the infection, an antimicrobial agent with anaerobic activity should be administered in combination with ZITHROMAX.

ZITHROMAX for injection should be followed by ZITHROMAX by the oral route as required. [see Dosage and Administration (2)]

1.3 Usage

To reduce the development of drug-resistant bacteria and maintain the effectiveness of ZITHROMAX (azithromycin) and other antibacterial drugs, ZITHROMAX (azithromycin) should be used only to treat infections that are proven or strongly suspected to be caused by susceptible bacteria. When culture and susceptibility information are available, they should be considered in selecting or modifying antibacterial therapy. In the absence of such data, local epidemiology and susceptibility patterns may contribute to the empiric selection of therapy.

2 DOSAGE AND ADMINISTRATION

[see Indications and Usage (1) and Clinical Pharmacology (12.3)]

2.1 Community-Acquired Pneumonia

The recommended dose of ZITHROMAX for injection for the treatment of adult patients with community-acquired pneumonia due to the indicated organisms is 500 mg as a single daily dose by the intravenous route for at least two days. Intravenous therapy should be followed by azithromycin by the oral route at a single, daily dose of 500 mg, administered as two 250 mg tablets to complete a 7- to 10-day course of therapy. The timing of the switch to oral therapy should be done at the discretion of the physician and in accordance with clinical response.

2.2 Pelvic Inflammatory Disease

The recommended dose of ZITHROMAX for injection for the treatment of adult patients with pelvic inflammatory disease due to the indicated organisms is 500 mg as a single daily dose by the intravenous route for one or two days. Intravenous therapy should be followed by azithromycin by the oral route at a single, daily dose of 250 mg to complete a 7-day course of therapy. The timing of the switch to oral therapy should be done at the discretion of the physician and in accordance with clinical response.

2.3 Preparation of the Solution for Intravenous Administration

The infusate concentration and rate of infusion for ZITHROMAX for injection should be either 1 mg/mL over 3 hr or 2 mg/mL over 1 hr. ZITHROMAX for injection should not be given as a bolus or as an intramuscular injection.

Reconstitution

Prepare the initial solution of ZITHROMAX for injection by adding 4.8 mL of Sterile Water for Injection to the 500 mg vial, and shaking the vial until all of the drug is dissolved. Since ZITHROMAX for injection is supplied under vacuum, it is recommended that a standard 5 mL (non-automated) syringe be used to ensure that the exact amount of 4.8 mL of Sterile Water is dispensed. Each mL of reconstituted solution contains 100 mg azithromycin. Reconstituted solution is stable for 24 hr when stored below 30°C (86°F).

Parenteral drug products should be inspected visually for particulate matter prior to administration. If particulate matter is evident in reconstituted fluids, the drug solution should be discarded.

Dilute this solution further prior to administration as instructed below.

Dilution

To provide azithromycin over a concentration range of 1–2 mg/mL, transfer 5 mL of the 100 mg/mL azithromycin solution into the appropriate amount of any of the diluents listed below:

Normal Saline (0.9% sodium chloride)
1/2 Normal Saline (0.45% sodium chloride)
5% Dextrose in Water
Lactated Ringer's Solution
5% Dextrose in 1/2 Normal Saline (0.45% sodium chloride) with 20 mEq KCl
5% Dextrose in Lactated Ringer's Solution
5% Dextrose in 1/3 Normal Saline (0.3% sodium chloride)
5% Dextrose in 1/2 Normal Saline (0.45% sodium chloride)
Normosol®-M in 5% Dextrose
Normosol®-R in 5% Dextrose

Final Infusion Solution Concentration (mg/mL) | Amount of Diluent (mL)
1 mg/mL | 500 mL
2 mg/mL | 250 mL

Other intravenous substances, additives, or medications should not be added to ZITHROMAX for injection, or infused simultaneously through the same intravenous line.

Storage

When diluted according to the instructions (1 mg/mL to 2 mg/mL), ZITHROMAX for injection is stable for 24 hr at or below room temperature 30°C (86°F), or for 7 days if stored under refrigeration 5°C (41°F).

3 DOSAGE FORMS AND STRENGTHS

ZITHROMAX for injection is supplied as white to off-white lyophilized powder in a single-dose vial equivalent to 500 mg of azithromycin for intravenous administration.

4 CONTRAINDICATIONS

4.1 Hypersensitivity

ZITHROMAX is contraindicated in patients with known hypersensitivity to azithromycin, erythromycin, any macrolide or ketolide drugs.

4.2 Hepatic Dysfunction

ZITHROMAX is contraindicated in patients with a history of cholestatic jaundice/hepatic dysfunction associated with prior use of azithromycin.

5 WARNINGS AND PRECAUTIONS

5.1 Hypersensitivity

Serious allergic reactions, including angioedema, anaphylaxis, and dermatologic reactions including Acute Generalized Exanthematous Pustulosis (AGEP), Stevens-Johnson Syndrome, and toxic epidermal necrolysis have been reported in patients on azithromycin therapy. [see Contraindications (4.1)]

Fatalities have been reported. Cases of Drug Reaction with Eosinophilia and Systemic Symptoms (DRESS) have also been reported. Despite initially successful symptomatic treatment of the allergic symptoms, when symptomatic therapy was discontinued, the allergic symptoms recurred soon thereafter in some patients without further azithromycin exposure. These patients required prolonged periods of observation and symptomatic treatment. The relationship of these episodes to the long tissue half-life of azithromycin and subsequent prolonged exposure to antigen is unknown at present.

If an allergic reaction occurs, the drug should be discontinued and appropriate therapy should be instituted. Physicians should be aware that the allergic symptoms may reappear after symptomatic therapy has been discontinued.

5.2 Hepatotoxicity

Abnormal liver function, hepatitis, cholestatic jaundice, hepatic necrosis, and hepatic failure have been reported, some of which have resulted in death. Discontinue azithromycin immediately if signs and symptoms of hepatitis occur.

5.3 Infantile Hypertrophic Pyloric Stenosis (IHPS)

Following the use of azithromycin in neonates (treatment up to 42 days of life), IHPS has been reported. Direct parents and caregivers to contact their physician if vomiting or irritability with feeding occurs.

5.4 QT Prolongation

Prolonged cardiac repolarization and QT interval, imparting a risk of developing cardiac arrhythmia and torsades de pointes, have been seen with treatment with macrolides, including azithromycin. Cases of torsades de pointes have been spontaneously reported during postmarketing surveillance in patients receiving azithromycin. Providers should consider the risk of QT prolongation, which can be fatal when weighing the risks and benefits of azithromycin for at-risk groups including:

- patients with known prolongation of the QT interval, a history of torsades de pointes, congenital long QT syndrome, bradyarrhythmias or uncompensated heart failure
- patients on drugs known to prolong the QT interval
- patients with ongoing proarrhythmic conditions such as uncorrected hypokalemia or hypomagnesemia, clinically significant bradycardia, and in patients receiving Class IA (quinidine, procainamide) or Class III (dofetilide, amiodarone, sotalol) antiarrhythmic agents.

Elderly patients may be more susceptible to drug-associated effects on the QT interval.

5.5 Cardiovascular Death

Some observational studies have shown an approximately two-fold increased short-term potential risk of acute cardiovascular death in adults exposed to azithromycin relative to other antibacterial drugs, including amoxicillin. The five-day cardiovascular mortality observed in these studies ranged from 20 to 400 per million azithromycin treatment courses. This potential risk was noted to be greater during the first five days of azithromycin use and does not appear to be limited to those patients with preexisting cardiovascular diseases. The data in these observational studies are insufficient to establish or exclude a causal relationship between acute cardiovascular death and azithromycin use. Consider balancing this potential risk with treatment benefits when prescribing ZITHROMAX.

5.6 Clostridioides difficile-Associated Diarrhea

Clostridioides difficile associated diarrhea (CDAD) has been reported with use of nearly all antibacterial agents, including ZITHROMAX (azithromycin for injection), and may range in severity from mild diarrhea to fatal colitis. Treatment with antibacterial agents alters the normal flora of the colon leading to overgrowth of C. difficile.

C. difficile produces toxins A and B which contribute to the development of CDAD. Hypertoxin producing strains of C. difficile cause increased morbidity and mortality, as these infections can be refractory to antibacterial therapy and may require colectomy. CDAD must be considered in all patients who present with diarrhea following antibacterial use. Careful medical history is necessary since CDAD has been reported to occur over two months after the administration of antibacterial agents.

If CDAD is suspected or confirmed, ongoing antibacterial use not directed against C. difficile may need to be discontinued. Appropriate fluid and electrolyte management, protein supplementation, antibacterial treatment of C. difficile, and surgical evaluation should be instituted as clinically indicated.

5.7 Exacerbation of Myasthenia Gravis

Exacerbations of symptoms of myasthenia gravis and new onset of myasthenic syndrome have been reported in patients receiving azithromycin therapy.

5.8 Infusion Site Reactions

ZITHROMAX for injection should be reconstituted and diluted as directed and administered as an intravenous infusion over not less than 60 minutes. [see Dosage and Administration (2)]

Local IV site reactions have been reported with the intravenous administration of azithromycin. The incidence and severity of these reactions were the same when 500 mg azithromycin was given over 1 hour (2 mg/mL as 250 mL infusion) or over 3 hr (1 mg/mL as 500 mL infusion) [see Adverse Reactions (6)]. All volunteers who received infusate concentrations above 2 mg/mL experienced local IV site reactions and, therefore, higher concentrations should be avoided.

5.9 Development of Drug-Resistant Bacteria

Prescribing ZITHROMAX in the absence of a proven or strongly suspected bacterial infection is unlikely to provide benefit to the patient and increases the risk of the development of drug-resistant bacteria.

6 ADVERSE REACTIONS

The following clinically significant adverse reactions are described elsewhere in labeling:

- Hypersensitivity [see Warnings and Precautions (5.1)]
- Hepatotoxicity [see Warnings and Precautions (5.2)]
- Infantile Hypertrophic Pyloric Stenosis (IHPS) [see Warnings and Precautions (5.3)]
- QT Prolongation [see Warnings and Precautions (5.4)]
- Cardiovascular Death [see Warnings and Precautions (5.5)]
- Clostridioides difficile-Associated Diarrhea (CDAD) [see Warnings and Precautions (5.6)]
- Exacerbation of Myasthenia Gravis [see Warnings and Precautions (5.7)]

6.1 Clinical Trials Experience

Because clinical trials are conducted under widely varying conditions, adverse reaction rates observed in the clinical trials of a drug cannot be directly compared to rates in the clinical trials of another drug and may not reflect the rates observed in practice.

In clinical trials of intravenous azithromycin for community-acquired pneumonia, in which 2 to 5 IV doses were given, the reported adverse reactions were mild to moderate in severity and were reversible upon discontinuation of the drug. The majority of patients in these trials had one or more co-morbid diseases and were receiving concomitant medications. Approximately 1.2% of the patients discontinued intravenous ZITHROMAX therapy, and a total of 2.4% discontinued azithromycin therapy by either the intravenous or oral route because of clinical or laboratory side effects.

In clinical trials conducted in patients with pelvic inflammatory disease, in which 1 to 2 IV doses were given, 2% of women who received monotherapy with azithromycin and 4% who received azithromycin plus metronidazole discontinued therapy due to clinical side effects.

Clinical adverse reactions leading to discontinuations from these studies were gastrointestinal (abdominal pain, nausea, vomiting, diarrhea), and rashes; laboratory side effects leading to discontinuation were increases in transaminase levels and/or alkaline phosphatase levels.

Overall, the most common adverse reactions associated with treatment in adult patients who received IV/Oral ZITHROMAX in studies of community-acquired pneumonia were related to the gastrointestinal system with diarrhea/loose stools (4.3%), nausea (3.9%), abdominal pain (2.7%), and vomiting (1.4%) being the most frequently reported.

Approximately 12% of patients experienced a side effect related to the intravenous infusion; most common were pain at the injection site (6.5%) and local inflammation (3.1%).

The most common adverse reactions associated with treatment in adult women who received IV/Oral ZITHROMAX in trials of pelvic inflammatory disease were related to the gastrointestinal system. Diarrhea (8.5%) and nausea (6.6%) were most commonly reported, followed by vaginitis (2.8%), abdominal pain (1.9%), anorexia (1.9%), rash and pruritus (1.9%). When azithromycin was co-administered with metronidazole in these trials, a higher proportion of women experienced adverse reactions of nausea (10.3%), abdominal pain (3.7%), vomiting (2.8%), infusion site reaction, stomatitis, dizziness, or dyspnea (all at 1.9%).

Adverse reactions that occurred with a frequency of 1% or less included the following:

Gastrointestinal: Dyspepsia, flatulence, mucositis, oral moniliasis, and gastritis.
Nervous system: Headache, somnolence.
Allergic: Bronchospasm.
Special senses: Taste perversion.

6.2 Postmarketing Experience

The following adverse reactions have been identified during post-approval use of azithromycin. Because these reactions are reported voluntarily from a population of uncertain size, it is not always possible to reliably estimate their frequency or establish a causal relationship to drug exposure.

Adverse reactions reported with azithromycin during the postmarketing period in adult and/or pediatric patients for which a causal relationship may not be established include:

Allergic: Arthralgia, edema, urticaria and angioedema.
Cardiovascular: Arrhythmias including ventricular tachycardia and hypotension. There have been reports of QT prolongation, torsades de pointes, and cardiovascular death.
Gastrointestinal: Anorexia, constipation, dyspepsia, flatulence, vomiting/diarrhea, pseudomembranous colitis, pancreatitis, oral candidiasis, pyloric stenosis, and reports of tongue discoloration.
General: Asthenia, paresthesia, fatigue, malaise and anaphylaxis (including fatalities).
Genitourinary: Interstitial nephritis and acute renal failure and vaginitis.
Hematopoietic: Thrombocytopenia.
Liver/biliary: Abnormal liver function, hepatitis, cholestatic jaundice, hepatic necrosis, and hepatic failure. [see Warnings and Precautions (5.2)]
Nervous system: Convulsions, dizziness/vertigo, headache, somnolence, hyperactivity, nervousness, agitation and syncope.
Psychiatric: Aggressive reaction and anxiety.
Skin/appendages: Pruritus, serious skin reactions including, erythema multiforme, AGEP, Stevens-Johnson syndrome, toxic epidermal necrolysis, and DRESS.
Special senses: Hearing disturbances including hearing loss, deafness and/or tinnitus and reports of taste/smell perversion and/or loss.

6.3 Laboratory Abnormalities

Significant abnormalities (irrespective of drug relationship) occurring during the clinical trials were reported as follows:

- elevated ALT (SGPT), AST (SGOT), creatinine (4 to 6%)
- elevated LDH, bilirubin (1 to 3%)
- leukopenia, neutropenia, decreased platelet count, and elevated serum alkaline phosphatase (less than 1%)

When follow-up was provided, changes in laboratory tests appeared to be reversible.

In multiple-dose clinical trials involving more than 750 patients treated with ZITHROMAX (IV/Oral), less than 2% of patients discontinued azithromycin therapy because of treatment-related liver enzyme abnormalities.

7 DRUG INTERACTIONS

7.1 Nelfinavir

Co-administration of nelfinavir at steady-state with a single oral dose of azithromycin resulted in increased azithromycin serum concentrations. Although a dose adjustment of azithromycin is not recommended when administered in combination with nelfinavir, close monitoring for known adverse reactions of azithromycin, such as liver enzyme abnormalities and hearing impairment, is warranted. [see Adverse Reactions (6)]

7.2 Warfarin

Spontaneous postmarketing reports suggest that concomitant administration of azithromycin may potentiate the effects of oral anticoagulants such as warfarin, although the prothrombin time was not affected in the dedicated drug interaction study with azithromycin and warfarin. Prothrombin times should be carefully monitored while patients are receiving azithromycin and oral anticoagulants concomitantly.

7.3 Potential Drug-Drug Interaction with Macrolides

Interactions with digoxin, colchicine or phenytoin have not been reported in clinical trials with azithromycin. No specific drug interaction studies have been performed to evaluate potential drug-drug interaction. However, drug interactions have been observed with other macrolide products. Until further data are developed regarding drug interactions when digoxin, colchicine or phenytoin are used with azithromycin careful monitoring of patients is advised.

8 USE IN SPECIFIC POPULATIONS

8.1 Pregnancy

Risk Summary

Available data from published literature and postmarketing experience over several decades with azithromycin use in pregnant women have not identified any drug-associated risks for major birth defects, miscarriage, or adverse maternal or fetal outcomes (see Data).

Developmental toxicity studies with azithromycin in rats, mice, and rabbits showed no drug-induced fetal malformations at doses up to 4, 2, and 2 times, respectively, an adult human daily dose of 500 mg based on body surface area. Decreased viability and delayed development were observed in the offspring of pregnant rats administered azithromycin from day 6 of pregnancy through weaning at a dose equivalent to 4 times an adult human daily dose of 500 mg based on body surface area (see Data).

The estimated background risk of major birth defects and miscarriage for the indicated populations is unknown. All pregnancies have a background risk of birth defect, loss, or other adverse outcomes. In the U.S. general population, the estimated background risk of major birth defects and miscarriage in clinically recognized pregnancies is 2 to 4% and 15 to 20%, respectively.

Data

Human Data

Available data from published observational studies, case series, and case reports over several decades do not suggest an increased risk for major birth defects, miscarriage, or adverse maternal or fetal outcomes with azithromycin use in pregnant women. Limitations of these data include the lack of randomization and inability to control for confounders such as underlying maternal disease and maternal use of concomitant medications.

Animal Data

Reproductive and developmental toxicology studies have not been conducted using IV administration of azithromycin to animals. Azithromycin administered during the period of organogenesis did not cause fetal malformations in rats and mice at oral doses up to 200 mg/kg/day (moderately maternally toxic). Based on body surface area, this dose is approximately 4 (rats) and 2 (mice) times an adult human daily dose of 500 mg. In rabbits administered azithromycin at oral doses of 10, 20, and 40 mg/kg/day during organogenesis, reduced maternal body weight and food consumption were observed in all groups; no evidence of fetotoxicity or teratogenicity was observed at these doses, the highest of which is estimated to be 2 times an adult human daily dose of 500 mg based on body surface area.

In a pre- and postnatal development study, azithromycin was administered orally to pregnant rats from day 6 of pregnancy until weaning at doses of 50 or 200 mg/kg/day. Maternal toxicity (reduced food consumption and body weight gain; increased stress at parturition) was observed at the higher dose. Effects in the offspring were noted at 200 mg/kg/day during the postnatal development period (decreased viability, delayed developmental landmarks). These effects were not observed in a pre- and postnatal rat study when up to 200 mg/kg/day of azithromycin was given orally beginning on day 15 of pregnancy until weaning.

8.2 Lactation

Risk Summary

Azithromycin is present in human milk (see Data). Non-serious adverse reactions have been reported in breastfed infants after maternal administration of azithromycin (see Clinical Considerations). There are no available data on the effects of azithromycin on milk production. The developmental and health benefits of breastfeeding should be considered along with the mother's clinical need for ZITHROMAX and any potential adverse effects on the breastfed infant from ZITHROMAX or from the underlying maternal condition.

Clinical Considerations

Advise women to monitor the breastfed infant for diarrhea, vomiting, or rash.

Data

Azithromycin breastmilk concentrations were measured in 20 women after receiving a single 2 g oral dose of azithromycin during labor. Breastmilk samples collected on days 3 and 6 postpartum as well as 2 and 4 weeks postpartum revealed the presence of azithromycin in breastmilk up to 4 weeks after dosing. In another study, a single dose of azithromycin 500 mg was administered intravenously to 8 women prior to incision for cesarean section. Breastmilk (colostrum) samples obtained between 12 and 48 hours after dosing revealed that azithromycin persisted in breastmilk up to 48 hours.

8.4 Pediatric Use

Safety and effectiveness of azithromycin for injection in children or adolescents under 16 years have not been established. In controlled clinical studies, azithromycin has been administered to pediatric patients (age 6 months to 16 years) by the oral route. For information regarding the use of ZITHROMAX (azithromycin for oral suspension) in the treatment of pediatric patients, [see Indications and Usage (1), and Dosage and Administration (2)] of the prescribing information for ZITHROMAX (azithromycin for oral suspension) 100 mg/5 mL and 200 mg/5 mL bottles.

8.5 Geriatric Use

Pharmacokinetic studies with intravenous azithromycin have not been performed in older volunteers. Pharmacokinetics of azithromycin following oral administration in older volunteers (65–85 years old) were similar to those in younger volunteers (18–40 years old) for the 5-day therapeutic regimen.

In multiple-dose clinical trials of intravenous azithromycin in the treatment of community-acquired pneumonia, 45% of patients (188/414) were at least 65 years of age and 22% of patients (91/414) were at least 75 years of age. No overall differences in safety were observed between these subjects and younger subjects in terms of adverse reactions, laboratory abnormalities, and discontinuations. Similar decreases in clinical response were noted in azithromycin- and comparator-treated patients with increasing age.

ZITHROMAX (azithromycin for injection) contains 114 mg (4.96 mEq) of sodium per vial. At the usual recommended doses, patients would receive 114 mg (4.96 mEq) of sodium. The geriatric population may respond with a blunted natriuresis to salt loading. The total sodium content from dietary and non-dietary sources may be clinically important with regard to such diseases as congestive heart failure.

Elderly patients may be more susceptible to development of torsades de pointes arrhythmias than younger patients. [see Warnings and Precautions (5.4)]

10 OVERDOSAGE

Adverse reactions experienced in higher than recommended doses were similar to those seen at normal doses particularly nausea, diarrhea, and vomiting. In the event of overdosage, general symptomatic and supportive measures are indicated as required.

11 DESCRIPTION

ZITHROMAX for injection contains the active ingredient azithromycin, an azalide, a subclass of macrolide antibacterial drug, for intravenous injection. Azithromycin has the chemical name (2R,3S,4R,5R,8R,10R,11R,12S,13S,14R)-13- [(2,6-dideoxy-3-C-methyl-3-O -methyl-α-L-ribo-hexopyranosyl)oxy]-2-ethyl-3,4,10-trihydroxy-3,5,6,8,10,12,14-hepta-methyl- 11- [[3,4,6-trideoxy-3-(dimethylamino)-β-D-xylo-hexopyranosyl]oxy]-1-oxa- 6-azacyclopentadecan-15-one. Azithromycin is derived from erythromycin; however, it differs chemically from erythromycin in that a methyl-substituted nitrogen atom is incorporated into the lactone ring. Its molecular formula is C38H72N2O12, and its molecular weight is 749. Azithromycin has the following structural formula:

Azithromycin, as the dihydrate, is a white crystalline powder with a molecular formula of C38H72N2O12∙ 2H2O and a molecular weight of 785.

ZITHROMAX for injection consists of azithromycin dihydrate and the following inactive ingredients: anhydrous citric acid and sodium hydroxide. Sodium hydroxide is added to adjust the pH. ZITHROMAX for injection is supplied as white to off-white lyophilized powder in a single-dose vial for intravenous administration. Each vial contains azithromycin dihydrate equivalent to 500 mg of azithromycin, 384.6 mg anhydrous citric acid, and sodium hydroxide. Reconstitution, according to label directions, results in approximately 5 mL of ZITHROMAX for intravenous injection with each mL containing azithromycin dihydrate equivalent to 100 mg of azithromycin, 76.9 mg anhydrous citric acid, and sodium hydroxide.

12 CLINICAL PHARMACOLOGY

12.1 Mechanism of Action

Azithromycin is a macrolide antibacterial drug [see Microbiology (12.4)]

12.2 Pharmacodynamics

Based on animal models of infection, the antibacterial activity of azithromycin appears to correlate with the ratio of area under the concentration-time curve to minimum inhibitory concentration (AUC/MIC) for certain pathogens (S. pneumoniae and S. aureus). The principal pharmacokinetic/pharmacodynamic parameter best associated with clinical and microbiological cure has not been elucidated in clinical trials with azithromycin.

Cardiac Electrophysiology

QTc interval prolongation was studied in a randomized, placebo-controlled parallel trial in 116 healthy subjects who received either chloroquine (1,000 mg) alone or in combination with oral azithromycin (500 mg, 1,000 mg, and 1,500 mg once daily). Co-administration of azithromycin increased the QTc interval in a dose- and concentration- dependent manner. In comparison to chloroquine alone, the maximum mean (95% upper confidence bound) increases in QTcF were 5 (10) ms, 7 (12) ms and 9 (14) ms with the co-administration of 500 mg, 1,000 mg and 1,500 mg azithromycin, respectively.

Since the mean Cmax of azithromycin following a 500 mg IV dose given over 1 hr is higher than the mean Cmax of azithromycin following the administration of a 1,500 mg oral dose, it is possible that QTc may be prolonged to a greater extent with IV azithromycin at close proximity to a one hour infusion of 500 mg.

12.3 Pharmacokinetics

In patients hospitalized with community-acquired pneumonia receiving single daily one-hour intravenous infusions for 2 to 5 days of 500 mg azithromycin at a concentration of 2 mg/mL, the mean Cmax ± S.D. achieved was 3.63 ± 1.60 mcg/mL, while the 24-hour trough level was 0.20 ± 0.15 mcg/mL, and the AUC24 was 9.60 ± 4.80 mcg∙hr/mL.

The mean Cmax, 24-hour trough and AUC24 values were 1.14 ± 0.14 mcg/mL, 0.18 ± 0.02 mcg/mL, and 8.03 ±0.86 mcg∙hr/mL, respectively, in normal volunteers receiving a 3-hour intravenous infusion of 500 mg azithromycin at a concentration of 1 mg/mL. Similar pharmacokinetic values were obtained in patients hospitalized with community-acquired pneumonia who received the same 3-hour dosage regimen for 2–5 days.

Infusion Concentration, Duration | Time after starting the infusion (hr)
Infusion Concentration, Duration | 0.5 | 1 | 2 | 3 | 4 | 6 | 8 | 12 | 24
2 mg/mL, 1 hr [500 mg (2 mg/mL) for 2–5 days in community-acquired pneumonia patients.] | 2.98 ±1.12 | 3.63 ±1.73 | 0.60 ±0.31 | 0.40 ±0.23 | 0.33 ±0.16 | 0.26 ±0.14 | 0.27±0.15 | 0.20 ±0.12 | 0.20 ±0.15
1 mg/mL, 3 hr [500 mg (1 mg/mL) for 5 days in healthy subjects.] | 0.91 ±0.13 | 1.02 ±0.11 | 1.14 ±0.13 | 1.13 ±0.16 | 0.32 ±0.05 | 0.28 ±0.04 | 0.27±0.03 | 0.22 ±0.02 | 0.18 ±0.02

Comparison of the plasma pharmacokinetic parameters following the 1st and 5th daily doses of 500 mg intravenous azithromycin showed only an 8% increase in Cmax but a 61% increase in AUC24 reflecting a threefold rise in C24 trough levels.

Following single-oral doses of 500 mg azithromycin (two 250 mg capsules) to 12 healthy volunteers, Cmax, trough level, and AUC24 were reported to be 0.41 mcg/mL, 0.05 mcg/mL, and 2.6 mcg∙hr/mL, respectively. These oral values are approximately 38%, 83%, and 52% of the values observed following a single 500-mg I.V. 3-hour infusion (Cmax: 1.08 mcg/mL, trough: 0.06 mcg/mL, and AUC24: 5 mcg∙hr/mL). Thus, plasma concentrations are higher following the intravenous regimen throughout the 24-hour interval.

Distribution

The serum protein binding of azithromycin is variable in the concentration range approximating human exposure, decreasing from 51% at 0.02 mcg/mL to 7% at 2 mcg/mL.

Tissue concentrations have not been obtained following intravenous infusions of azithromycin, but following oral administration in humans azithromycin has been shown to penetrate into tissues, including skin, lung, tonsil, and cervix.

Tissue levels were determined following a single oral dose of 500 mg azithromycin in 7 gynecological patients. Approximately 17 hr after dosing, azithromycin concentrations were 2.7 mcg/g in ovarian tissue, 3.5 mcg/g in uterine tissue, and 3.3 mcg/g in salpinx. Following a regimen of 500 mg on the first day followed by 250 mg daily for 4 days, concentrations in the cerebrospinal fluid were less than 0.01 mcg/mL in the presence of non-inflamed meninges.

Metabolism

In vitro and in vivo studies to assess the metabolism of azithromycin have not been performed.

Elimination

Plasma concentrations of azithromycin following single 500 mg oral and IV doses declined in a polyphasic pattern with a mean apparent plasma clearance of 630 mL/min and terminal elimination half-life of 68 hr. The prolonged terminal half-life is thought to be due to extensive uptake and subsequent release of drug from tissues.

In a multiple-dose study in 12 normal volunteers utilizing a 500 mg (1 mg/mL) one-hour intravenous-dosage regimen for five days, the amount of administered azithromycin dose excreted in urine in 24 hr was about 11% after the 1st dose and 14% after the 5th dose. These values are greater than the reported 6% excreted unchanged in urine after oral administration of azithromycin. Biliary excretion is a major route of elimination for unchanged drug, following oral administration.

Specific Populations

Patients with Renal Impairment

Azithromycin pharmacokinetics were investigated in 42 adults (21 to 85 years of age) with varying degrees of renal impairment. Following the oral administration of a single 1,000 mg dose of azithromycin, mean Cmax and AUC0–120 increased by 5.1% and 4.2%, respectively in subjects with mild to moderate renal impairment (GFR 10 to 80 mL/min) compared to subjects with normal renal function (GFR >80 mL/min). The mean Cmax and AUC0–120 increased 61% and 35%, respectively in subjects with severe renal impairment (GFR <10 mL/min) compared to subjects with normal renal function (GFR >80 mL/min).

Patients with Hepatic Impairment

The pharmacokinetics of azithromycin in subjects with hepatic impairment has not been established.

Male and Female Patients

There are no significant differences in the disposition of azithromycin between male and female subjects. No dosage adjustment is recommended based on gender.

Geriatric Patients

Pharmacokinetic studies with intravenous azithromycin have not been performed in older volunteers. Pharmacokinetics of azithromycin following oral administration in older volunteers (65–85 years old) were similar to those in younger volunteers (18–40 years old) for the 5-day therapeutic regimen. [see Geriatric Use 8.5)].

Pediatric Patients

Pharmacokinetic studies with intravenous azithromycin have not been performed in children.

Drug Interaction Studies

Drug interaction studies were performed with oral azithromycin and other drugs likely to be co-administered. The effects of co-administration of azithromycin on the pharmacokinetics of other drugs are shown in Table 1 and the effects of other drugs on the pharmacokinetics of azithromycin are shown in Table 2.

Co-administration of azithromycin at therapeutic doses had a modest effect on the pharmacokinetics of the drugs listed in Table 1. No dosage adjustment of drugs listed in Table 1 is recommended when co-administered with azithromycin.

Co-administration of azithromycin with efavirenz or fluconazole had a modest effect on the pharmacokinetics of azithromycin. Nelfinavir significantly increased the Cmax and AUC of azithromycin. No dosage adjustment of azithromycin is recommended when administered with drugs listed in Table 2 [see Drug Interactions (7.3)].

Table 1. Drug Interactions: Pharmacokinetic Parameters for Co-administered Drugs in the Presence of Azithromycin
Co-administered Drug | Dose of Co-administered Drug | Dose of Azithromycin | n | Ratio (with/without azithromycin) of Co-administered Drug Pharmacokinetic Parameters (90% CI); No Effect = 1
 |  |  |  | Mean Cmax | Mean AUC
Atorvastatin | 10 mg/day for 8 days | 500 mg/day orally on days 6–8 | 12 | 0.83 (0.63 to 1.08) | 1.01 (0.81 to 1.25)
Carbamazepine | 200 mg/day for 2 days, then 200 mg twice a day for 18 days | 500 mg/day orally for days 16–18 | 7 | 0.97 (0.88 to 1.06) | 0.96 (0.88 to 1.06)
Cetirizine | 20 mg/day for 11 days | 500 mg orally on day 7, then 250 mg/day on days 8–11 | 14 | 1.03 (0.93 to 1.14) | 1.02 (0.92 to 1.13)
Didanosine | 200 mg orally twice a day for 21 days | 1,200 mg/day orally on days 8–21 | 6 | 1.44 (0.85 to 2.43) | 1.14 (0.83 to 1.57)
Efavirenz | 400 mg/day for 7 days | 600 mg orally on day 7 | 14 | 1.04 [- 90% Confidence interval not reported] | 0.95
Fluconazole | 200 mg orally single dose | 1,200 mg orally single dose | 18 | 1.04 (0.98 to 1.11) | 1.01 (0.97 to 1.05)
Indinavir | 800 mg three times a day for 5 days | 1,200 mg orally on day 5 | 18 | 0.96 (0.86 to 1.08) | 0.9 (0.81 to 1)
Midazolam | 15 mg orally on day 3 | 500 mg/day orally for 3 days | 12 | 1.27 (0.89 to 1.81) | 1.26 (1.01 to 1.56)
Nelfinavir | 750 mg three times a day for 11 days | 1,200 mg orally on day 9 | 14 | 0.9 (0.81 to 1.01) | 0.85 (0.78 to 0.93)
Sildenafil | 100 mg on days 1 and 4 | 500 mg/day orally for 3 days | 12 | 1.16 (0.86 to 1.57) | 0.92 (0.75 to 1.12)
Theophylline | 4 mg/kg IV on days 1, 11, 25 | 500 mg orally on day 7, 250 mg/day on days 8–11 | 10 | 1.19 (1.02 to 1.4) | 1.02 (0.86 to 1.22)
Theophylline | 300 mg orally BID ×15 days | 500 mg orally on day 6, then 250 mg/day on days 7–10 | 8 | 1.09 (0.92 to 1.29) | 1.08 (0.89 to 1.31)
Triazolam | 0.125 mg on day 2 | 500 mg orally on day 1, then 250 mg/day on day 2 | 12 | 1.06 | 1.02
Trimethoprim/Sulfamethoxazole | 160 mg/800 mg/day orally for 7 days | 1,200 mg orally on day 7 | 12 | 0.85 (0.75 to 0.97)/ 0.9 (0.78 to 1.03) | 0.87 (0.8 to 0.95/ 0.96 (0.88 to 1.03)
Zidovudine | 500 mg/day orally for 21 days | 600 mg/day orally for 14 days | 5 | 1.12 (0.42 to 3.02) | 0.94 (0.52 to 1.7)
Zidovudine | 500 mg/day orally for 21 days | 1,200 mg/day orally for 14 days | 4 | 1.31 (0.43 to 3.97) | 1.3 (0.69 to 2.43)

Table 2. Drug Interactions: Pharmacokinetic Parameters for Azithromycin in the Presence of Co-administered Drugs [see Drug Interactions (7.3)].
Co-administered Drug | Dose of Co-administered Drug | Dose of Azithromycin | n | Ratio (with/without co-administered drug) of Azithromycin Pharmacokinetic Parameters (90% CI); No Effect = 1
 |  |  |  | Mean Cmax | Mean AUC
Efavirenz | 400 mg/day for 7 days | 600 mg orally on day 7 | 14 | 1.22 (1.04 to 1.42) | 0.92 [- 90% Confidence interval not reported]
Fluconazole | 200 mg orally single dose | 1,200 mg orally single dose | 18 | 0.82 (0.66 to 1.02) | 1.07 (0.94 to 1.22)
Nelfinavir | 750 mg three times a day for 11 days | 1,200 mg orally on day 9 | 14 | 2.36 (1.77 to 3.15) | 2.12 (1.80 to 2.5)

12.4 Microbiology

Mechanism of Action

Azithromycin acts by binding to the 23S rRNA of the 50S ribosomal subunit of susceptible microorganisms inhibiting bacterial protein synthesis and impeding the assembly of the 50S ribosomal subunit.

Resistance

Azithromycin demonstrates cross-resistance with erythromycin. The most frequently encountered mechanism of resistance to azithromycin is modification of the 23S rRNA target, most often by methylation. Ribosomal modifications can determine cross resistance to other macrolides, lincosamides and streptogramin B (MLSB phenotype).

Antimicrobial Activity

Azithromycin has been shown to be active against the following microorganisms, both in vitro and in clinical infections. [see Indications and Usage (1)]

Gram-positive Bacteria
Staphylococcus aureus
Streptococcus pneumoniae

Gram-negative Bacteria
Haemophilus influenzae
Moraxella catarrhalis
Neisseria gonorrhoeae
Legionella pneumophila

Other Bacteria
Chlamydophila pneumoniae
Chlamydia trachomatis
Mycoplasma hominis
Mycoplasma pneumoniae

The following in vitro data are available, but their clinical significance is unknown. At least 90 percent of the following bacteria exhibit an in vitro minimum inhibitory concentration (MIC) less than or equal to the susceptible breakpoint for azithromycin against isolates of similar genus or organism group. However, the efficacy of azithromycin in treating clinical infections caused by these bacteria has not been established in adequate and well-controlled clinical trials.

Aerobic Gram-Positive Bacteria
Streptococci (Groups C, F, G)
Viridans group streptococci

Gram-Negative Bacteria
Bordetella pertussis

Anaerobic Bacteria
Peptostreptococcus species
Prevotella bivia

Other Bacteria
Ureaplasma urealyticum

Susceptibility Testing

For specific information regarding susceptibility test interpretive criteria and associated test methods and quality control standards recognized by FDA for this drug, please see: https://www.fda.gov/STIC.

13 NONCLINICAL TOXICOLOGY

13.1 Carcinogenesis, Mutagenesis, Impairment of Fertility

Long-term studies in animals have not been performed to evaluate carcinogenic potential. Azithromycin has shown no mutagenic potential in standard laboratory tests: mouse lymphoma assay, human lymphocyte clastogenic assay, and mouse bone marrow clastogenic assay. In fertility studies conducted in male and female rats, oral administration of azithromycin for 64 to 66 days (males) or 15 days (females) prior to and during cohabitation resulted in decreased pregnancy rate at 20 and 30 mg/kg/day when both males and females were treated with azithromycin. This minimal effect on pregnancy rate (approximately 12% reduction compared to concurrent controls) did not become more pronounced when the dose was increased from 20 to 30 mg/kg/day (approximately 0.4 to 0.6 times the adult daily dose of 500 mg based on body surface area) and it was not observed when only one animal in the mated pair was treated. There were no effects on any other reproductive parameters, and there were no effects on fertility at 10 mg/kg/day. The relevance of these findings to patients being treated with azithromycin at the doses and durations recommended in the prescribing information is uncertain.

13.2 Animal Toxicology and/or Pharmacology

Phospholipidosis (intracellular phospholipid accumulation) has been observed in some tissues of mice, rats, and dogs given multiple oral doses of azithromycin. It has been demonstrated in numerous organ systems (e.g., eye, dorsal root ganglia, liver, gallbladder, kidney, spleen, and/or pancreas) in dogs and rats treated with azithromycin at doses which, expressed on the basis of body surface area, are similar to or less than the highest recommended adult human dose. This effect has been shown to be reversible after cessation of azithromycin treatment. Based on the pharmacokinetic data, phospholipidosis has been seen in the rat (50 mg/kg/day dose) at the observed maximal plasma concentration of 1.3 mcg/mL (1.6 times the observed Cmax of 0.821 mcg /mL at the adult dose of 2 g.) Similarly, it has been shown in the dog (10 mg/kg/day dose) at the observed maximal serum concentration of 1 mcg /mL (1.2 times the observed Cmax of 0.821 mcg /mL at the adult dose of 2 g).

Phospholipidosis was also observed in neonatal rats dosed for 18 days at 30 mg/kg/day, which is less than the pediatric dose of 60 mg/kg based on body surface area. It was not observed in neonatal rats treated for 10 days at 40 mg/kg/day with mean maximal serum concentrations of 1.86 mcg/mL, approximately 1.5 times the Cmax of 1.27 mcg/mL at the pediatric dose. Phospholipidosis has been observed in neonatal dogs (10 mg/kg/day) at maximum mean whole blood concentrations of 3.54 mcg/mL, approximately 3 times the pediatric dose Cmax. The significance of the findings for animals and for humans is unknown.

14 CLINICAL STUDIES

14.1 Community-Acquired Pneumonia

In a controlled trial of community-acquired pneumonia performed in the U.S., azithromycin (500 mg as a single daily dose by the intravenous route for 2 to 5 days, followed by 500 mg/day by the oral route to complete 7 to 10 days therapy) was compared to cefuroxime (2,250 mg/day in three divided doses by the intravenous route for 2 to 5 days followed by 1,000 mg/day in two divided doses by the oral route to complete 7 to 10 days therapy), with or without erythromycin. For the 291 patients who were evaluable for clinical efficacy, the clinical outcome rates, i.e., cure, improved, and success (cure + improved) among the 277 patients seen at 10 to 14 days post-therapy were as follows:

Clinical Outcome | Azithromycin | Comparator
Cure | 46% | 44%
Improved | 32% | 30%
Success (Cure + Improved) | 78% | 74%

In a separate, uncontrolled clinical and microbiological trial performed in the U.S., 94 patients with community-acquired pneumonia who received azithromycin in the same regimen were evaluable for clinical efficacy. The clinical outcome rates, i.e., cure, improved, and success (cure + improved) among the 84 patients seen at 10 to 14 days post-therapy were as follows:

Clinical Outcome | Azithromycin
Cure | 60%
Improved | 29%
Success (Cure + Improved) | 89%

Microbiological determinations in both trials were made at the pre-treatment visit and, where applicable, were reassessed at later visits. Serological testing was done on baseline and final visit specimens. The following combined presumptive bacteriological eradication rates were obtained from the evaluable groups:

Combined Bacteriological Eradication Rates for Azithromycin:

(at last completed visit) | Azithromycin
S. pneumoniae | 64/67 (96%) [Nineteen of twenty-four patients (79%) with positive blood cultures for S. pneumoniae were cured (intent-to-treat analysis) with eradication of the pathogen.]
H. influenzae | 41/43 (95%)
M. catarrhalis | 9/10 (90%)
S. aureus | 9/10 (90%)

The presumed bacteriological outcomes at 10 to 14 days post-therapy for patients treated with azithromycin with evidence (serology and/or culture) of atypical pathogens for both trials were as follows:

Evidence of Infection | Total | Cure | Improved | Cure + Improved
Mycoplasma pneumoniae | 18 | 11 (61%) | 5 (28%) | 16 (89%)
Chlamydia pneumoniae | 34 | 15 (44%) | 13 (38%) | 28 (82%)
Legionella pneumophila | 16 | 5 (31%) | 8 (50%) | 13 (81%)

16 HOW SUPPLIED/STORAGE AND HANDLING

ZITHROMAX for injection is supplied as white to off-white lyophilized powder under a vacuum in a single-dose vial equivalent to 500 mg of azithromycin for intravenous administration.

These are packaged as follows:

Unit of Sale | Concentration
NDC 0069-3150-83 | 500 mg/vial
Carton containing 10 single-dose vials

Before reconstitution, store vials at or below 30°C (86°F) [see Dosage and Administration (2.3)].

17 PATIENT COUNSELING INFORMATION

Patients should be informed of the following serious and potentially serious adverse reactions that have been associated with ZITHROMAX®

Diarrhea: Inform patients that diarrhea is a common problem caused by antibacterial drugs which usually ends when the antibacterial is discontinued. Sometimes after starting treatment with antibacterials, patients can develop watery and bloody stools (with or without stomach cramps and fever) even as late as two or more months after having taken the last dose of the antibacterial. If this occurs, patients should notify their physician as soon as possible.

This product's label may have been updated. For current full prescribing information, please visit www.pfizer.com.

LAB-0024-23.0

PRINCIPAL DISPLAY PANEL - 500 mg Vial Label

Single-Dose Vial
NDC 0069-3150-84

Zithromax®
(azithromycin) for injection

500 mg/vial

For I.V. infusion only

Rx only

STERILE
equivalent to 500 mg/vial of azithromycin

No Latex
No Preservative

Pfizer Injectables

PRINCIPAL DISPLAY PANEL - 500 mg Vial Carton

10 Single-Dose Vials

NDC 0069-3150-83
Contains 10 of NDC 0069-3150-84

Zithromax®
(azithromycin) for injection

Rx only

500 mg/vial

STERILE

For I.V. infusion only
Equivalent to 500 mg/vial of azithromycin
To yield 100 mg/mL* of solution when reconstituted as directed

No Latex
No Preservative

Pfizer Injectables